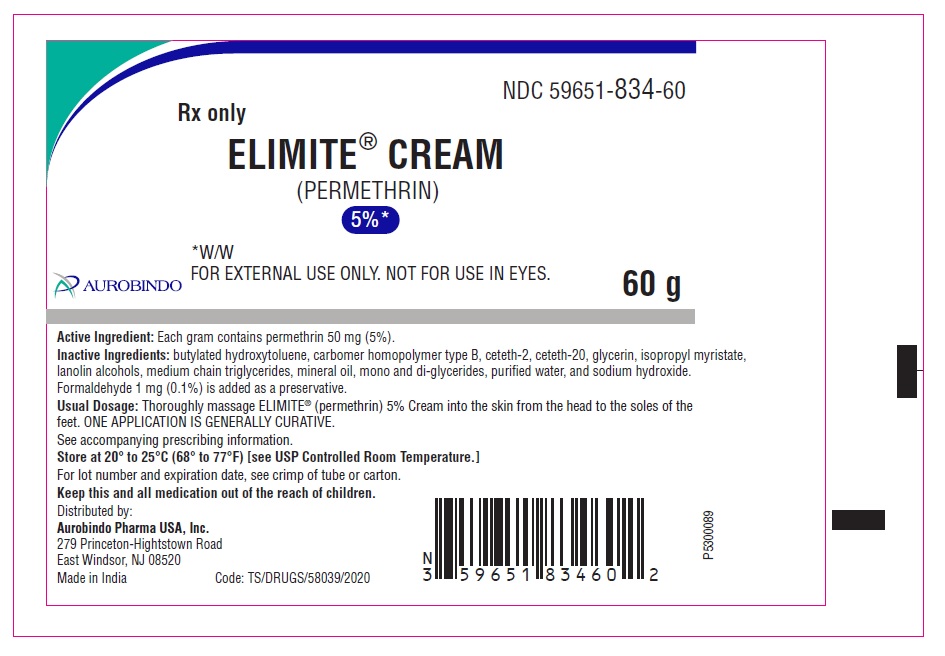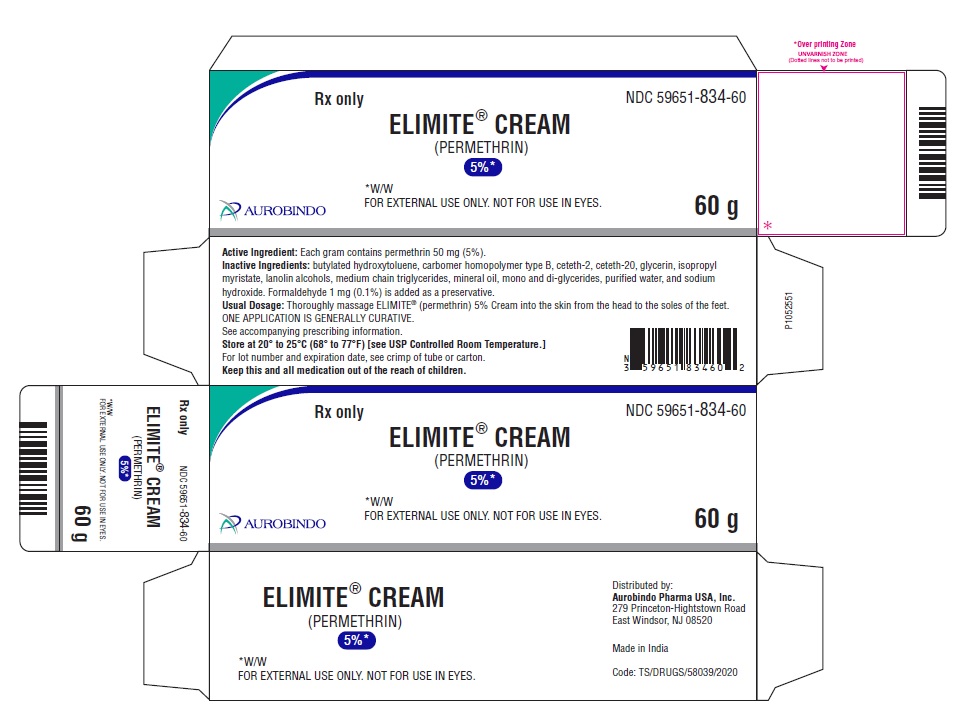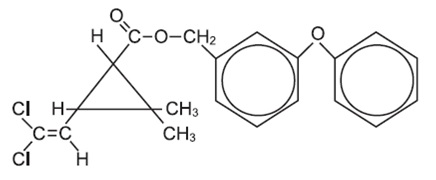 DRUG LABEL: ELIMITE
NDC: 59651-834 | Form: CREAM
Manufacturer: Aurobindo Pharma Limited
Category: prescription | Type: Human Prescription Drug Label
Date: 20240124

ACTIVE INGREDIENTS: PERMETHRIN 50 mg/1 g
INACTIVE INGREDIENTS: BUTYLATED HYDROXYTOLUENE; CARBOMER HOMOPOLYMER TYPE B (ALLYL PENTAERYTHRITOL CROSSLINKED); CETETH-2; CETETH-20; GLYCERIN; ISOPROPYL MYRISTATE; LANOLIN ALCOHOLS; MEDIUM-CHAIN TRIGLYCERIDES; MINERAL OIL; GLYCERYL MONO AND DIPALMITOSTEARATE; WATER; SODIUM HYDROXIDE; FORMALDEHYDE

ELIMITE® CREAM

(PERMETHRIN) 5%* *W/W

Rx only

DESCRIPTION

ELIMITE® (permethrin) 5% Cream is a topical scabicidal agent for the treatment of infestation with Sarcoptes scabiei (scabies). It is available in an off-white, greaseless, uniform mass. ELIMITE® (permethrin) 5% Cream is for topical use only.
Chemical Name - The permethrin used is an approximate 1:3 mixture of the cis and trans isomers of the pyrethroid 3-(2,2-dichloroethenyl)-2,2-dimethylcyclopropanecarboxylic acid, (3-phenoxyphenyl) methyl ester. Permethrin has a molecular formula of C21H20CI2O3 and a molecular weight of 391.29. It is a colorless or slightly brownish viscous liquid, semi-solid or crystalline solid.

Active Ingredient - Each gram contains permethrin 50 mg (5%).

Inactive Ingredients - Butylated hydroxytoluene, carbomer homopolymer type B, ceteth-2, ceteth-20, glycerin, isopropyl myristate, lanolin alcohols, medium chain triglycerides, mineral oil, mono and di-glycerides, purified water, and sodium hydroxide. Formaldehyde 1 mg (0.1%) is added as a preservative.

CLINICAL PHARMACOLOGY

Permethrin, a pyrethroid, is active against a broad range of pests including lice, ticks, fleas, mites, and other arthropods. It acts on the nerve cell membrane to disrupt the sodium channel current by which the polarization of the membrane is regulated. Delayed repolarization and paralysis of the pests are the consequences of this disturbance.

Permethrin is rapidly metabolized by ester hydrolysis to inactive metabolites which are excreted primarily in the urine. Although the amount of permethrin absorbed after a single application of the 5% cream has not been determined precisely, data from studies with ^14C-labeled permethrin and absorption studies of the cream applied to patients with moderate to severe scabies indicate it is 2% or less of the amount applied.

INDICATIONS AND USAGE

ELIMITE® (permethrin) 5% Cream is indicated for the treatment of infestation with Sarcoptes scabiei (scabies).

CONTRAINDICATIONS

ELIMITE® (permethrin) 5% Cream is contraindicated in patients with known hypersensitivity to any of its components, to any synthetic pyrethroid or pyrethrin.

WARNINGS

If hypersensitivity to ELIMITE® (permethrin) 5% Cream occurs, discontinue use.

PRECAUTIONS

GENERAL PRECAUTIONS

General - Scabies infestation is often accompanied by pruritus, edema, and erythema. Treatment with ELIMITE® (permethrin) 5% Cream may temporarily exacerbate these conditions.

PATIENT COUNSELING INFORMATION

Information for Patients - Patients with scabies should be advised that itching, mild burning and/or stinging may occur after application of ELIMITE® (permethrin) 5% Cream. In clinical trials, approximately 75% of patients treated with ELIMITE® (permethrin) 5% Cream who continued to manifest pruritus at 2 weeks had cessation by 4 weeks. If irritation persists, they should consult their physician. ELIMITE® (permethrin) 5% Cream may be very mildly irritating to the eyes. Patients should be advised to avoid contact with eyes during application and to flush with water immediately if ELIMITE® (permethrin) 5% Cream gets in the eyes.

CARCINOGENESIS AND MUTAGENESIS AND IMPAIRMENT OF FERTILITY

Carcinogenesis, Mutagenesis, Impairment of Fertility - Six carcinogenicity bioassays were evaluated with permethrin, three each in rats and mice. No tumorigenicity was seen in the rat studies. However, species-specific increases in pulmonary adenomas, a common benign tumor of mice of high spontaneous background incidence, were seen in the three mouse studies. In one of these studies there was an increased incidence of pulmonary alveolar-cell carcinomas and benign liver adenomas only in female mice when permethrin was given in their food at a concentration of 5000 ppm. Mutagenicity assays, which give useful correlative data for interpreting results from carcinogenicity bioassays in rodents, were negative. Permethrin showed no evidence of mutagenic potential in a battery of in vitro and in vivo genetic toxicity studies.

Permethrin did not have any adverse effect on reproductive function at a dose of 180 mg/kg/day orally in a three-generation rat study.

PREGNANCY

Pregnancy - Reproduction studies have been performed in mice, rats, and rabbits (200 to 400 mg/kg/day orally) and have revealed no evidence of impaired fertility or harm to the fetus due to permethrin. There are, however, no adequate and well-controlled studies in pregnant women. Because animal reproduction studies are not always predictive of human response, this drug should be used during pregnancy only if clearly needed.

NURSING MOTHERS

Nursing Mothers - It is not known whether this drug is excreted in human milk. Because many drugs are excreted in human milk and because of the evidence for tumorigenic potential of permethrin in animal studies, consideration should be given to discontinuing nursing temporarily or withholding the drug while the mother is nursing.

PEDIATRIC USE

Pediatric Use - ELIMITE® (permethrin) 5% Cream is safe and effective in pediatric patients two months of age and older. Safety and effectiveness in infants less than two months of age have not been established.

GERIATRIC USE

Geriatric Use - Clinical studies of ELIMITE® (permethrin) 5% Cream did not identify sufficient numbers of subjects aged 65 and over to allow a definitive statement regarding whether elderly subjects respond differently from younger subjects. Other reported clinical experience has not identified differences in responses between the elderly and younger patients. This drug is known to be substantially excreted by the kidney. However, since topical permethrin is metabolized in the liver and excreted in the urine as inactive metabolites, there does not appear to be an increased risk of toxic reactions in patients with impaired renal function when used as labeled.

ADVERSE REACTIONS

In clinical trials, generally mild and transient burning and stinging followed application with ELIMITE® (permethrin) 5% Cream in 10% of patients and was associated with the severity of infestation. Pruritus was reported in 7% of patients at various times post-application. Erythema, numbness, tingling, and rash were reported in 1 to 2% or less of patients (see PRECAUTIONS: General). Other adverse events reported since marketing ELIMITE® (permethrin) 5% Cream include: headache, fever, dizziness, abdominal pain, diarrhea and nausea and/or vomiting. Although extremely uncommon and not expected when used as directed (see DOSAGE AND ADMINISTRATION), rare occurrences of seizure have been reported. None have been medically confirmed as associated with ELIMITE® treatment.

OVERDOSAGE

No instance of accidental ingestion of ELIMITE® (permethrin) 5% Cream has been reported. If ingested, gastric lavage and general supportive measures should be employed. Excessive topical use (see DOSAGE AND ADMINISTRATION) may result in increased irritation and erythema.

DOSAGE AND ADMINISTRATION

Adults and Children - Thoroughly massage ELIMITE® (permethrin) 5% Cream into the skin from the head to the soles of the feet. Scabies rarely infests the scalp of adults, although the hairline, neck, temple, and forehead may be infested in infants and geriatric patients. Usually 30 grams is sufficient for an average adult. The cream should be removed by washing (shower or bath) after 8 to 14 hours. Infants should be treated on the scalp, temple, and forehead. ONE APPLICATION IS GENERALLY CURATIVE.

Patients may experience persistent pruritus after treatment. This is rarely a sign of treatment failure and is not an indication for retreatment. Demonstrable living mites after 14 days indicate that retreatment is necessary.

HOW SUPPLIED

ELIMITE® Cream, 5% contains 50 mg permethrin per gram. The off-white, greaseless, uniform mass is available as follows:

Carton containing one 60 g tube NDC 59651-834-60

STORAGE: Store at 20° to 25°C (68° to 77°F) [see USP Controlled Room Temperature.]

Distributed by:
Aurobindo Pharma USA, Inc.
279 Princeton-Hightstown Road
East Windsor, NJ 08520
Manufactured by:
Aurobindo Pharma Limited
Hyderabad-500 032, India
Revised: 11/2023

PACKAGE LABEL-PRINCIPAL DISPLAY PANEL - 5% Container Label (60 g Tube)

NDC 59651-834-60
Rx only
ELIMITE® CREAM
(PERMETHRIN)
5%*
*W/W
FOR EXTERNAL USE ONLY. NOT FOR USE IN EYES.
AUROBINDO 60 g

PACKAGE LABEL-PRINCIPAL DISPLAY PANEL - 5% Container Carton Label (60 g Tube)

NDC 59651-834-60
Rx only
ELIMITE® CREAM
(PERMETHRIN)
5%*
*W/W
FOR EXTERNAL USE ONLY. NOT FOR USE IN EYES.
AUROBINDO 60 g